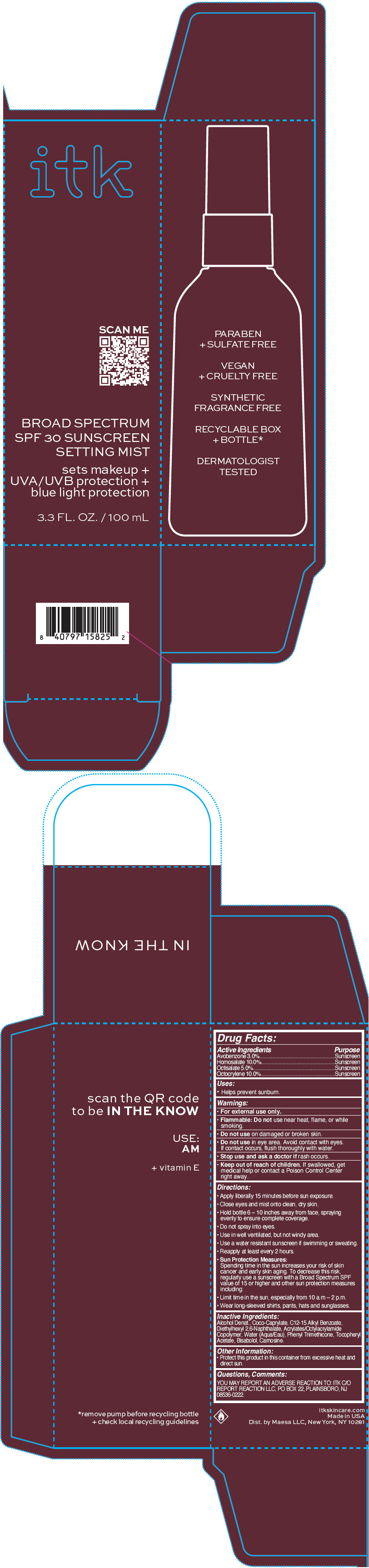 DRUG LABEL: ITK Broad spectrum SPF 30 Sunscreen
NDC: 71899-065 | Form: SPRAY
Manufacturer: MAESA, LLC.
Category: otc | Type: HUMAN OTC DRUG LABEL
Date: 20220411

ACTIVE INGREDIENTS: Avobenzone 3 mg/100 mL; Homosalate 10 mg/100 mL; Octisalate 5 mg/100 mL; Octocrylene 10 mg/100 mL
INACTIVE INGREDIENTS: ALCOHOL; Coco-Caprylate; ALKYL (C12-15) BENZOATE; Diethylhexyl 2,6-Naphthalate; ACRYLATE/ISOBUTYL METHACRYLATE/N-TERT-OCTYLACRYLAMIDE COPOLYMER (75000 MW); WATER; Phenyl Trimethicone; .ALPHA.-TOCOPHEROL ACETATE; LEVOMENOL; Carnosine

ITK Broad spectrum SPF 30 Sunscreen

Drug Facts:

ACTIVE INGREDIENT

Active Ingredients | Purpose
Avobenzone 3.0% | Sunscreen
Homosalate 10.0% | Sunscreen
Octisalate 5.0% | Sunscreen
Octocrylene 10.0% | Sunscreen

Uses

- Helps prevent sunburn.

Warnings

- For external use only.
- Flammable: Do not use near heat, flame, or while smoking.

- Do not use on damaged or broken skin.
- Do not use in eye area. Avoid contact with eyes. If contact occurs, flush thoroughly with water.

- Stop use and ask a doctor if rash occurs.

- Keep out of reach of children. If swallowed, get medical help or contact a Poison Control Center right away.

Directions

- Apply liberally 15 minutes before sun exposure.
- Close eyes and mist onto clean, dry skin.
- Hold bottle 6 – 10 inches away from face, spraying evenly to ensure complete coverage.
- Do not spray into eyes.
- Use in well ventilated, but not windy area.
- Use a water resistant sunscreen if swimming or sweating.
- Reapply at least every 2 hours.
- Sun Protection Measures:
  Spending time in the sun increases your risk of skin cancer and early skin aging. To decrease this risk, regularly use a sunscreen with a Broad Spectrum SPF value of 15 or higher and other sun protection measures including:
  - Limit time in the sun, especially from 10 a.m – 2 p.m.
  - Wear long-sleeved shirts, pants, hats and sunglasses.

Inactive Ingredients

Alcohol Denat., Coco-Caprylate, C12-15 Alkyl Benzoate, Diethylhexyl 2,6-Naphthalate, Acrylates/Octylacrylamide Copolymer, Water (Aqua/Eau), Phenyl Trimethicone, Tocopheryl Acetate, Bisabolol, Carnosine.

Other Information

- Protect this product in this container from excessive heat and direct sun.

Questions, Comments

YOU MAY REPORT AN ADVERSE REACTION TO: ITK C/O REPORT REACTION LLC, PO BOX 22, PLAINSBORO, NJ 08536-0222.

Dist. by Maesa LLC, New York, NY 10281

PRINCIPAL DISPLAY PANEL - 100 mL Bottle Carton

itk

SCAN ME

BROAD SPECTRUM
SPF 30 SUNSCREEN
SETTING MIST

sets makeup +
UVA/UVB protection +
blue light protection

3.3 FL. OZ. / 100 mL